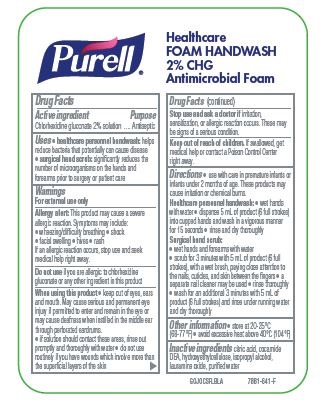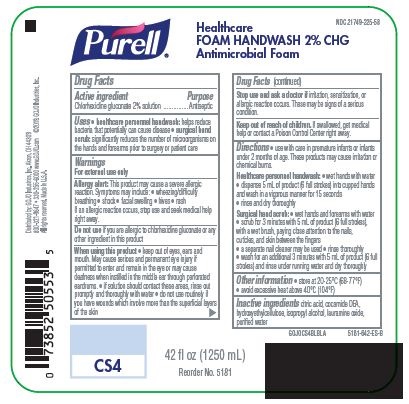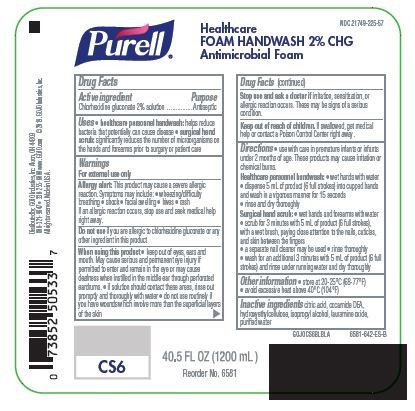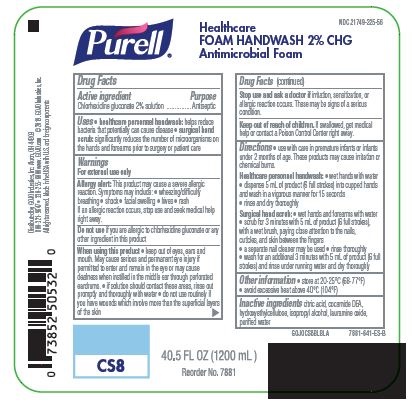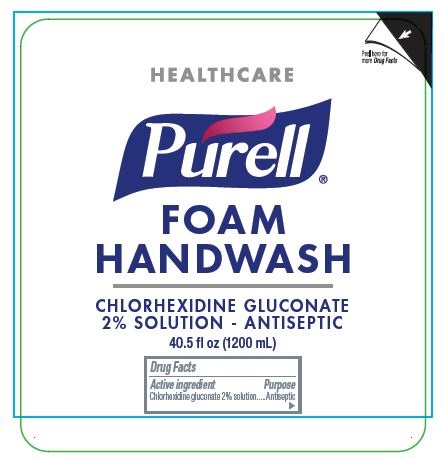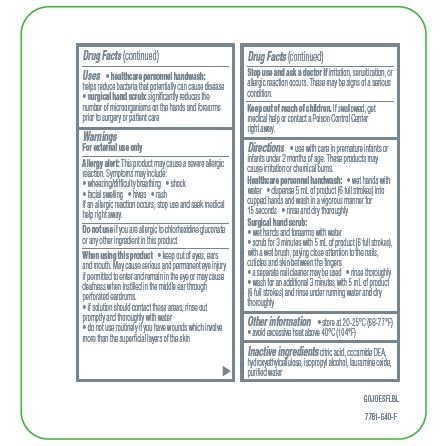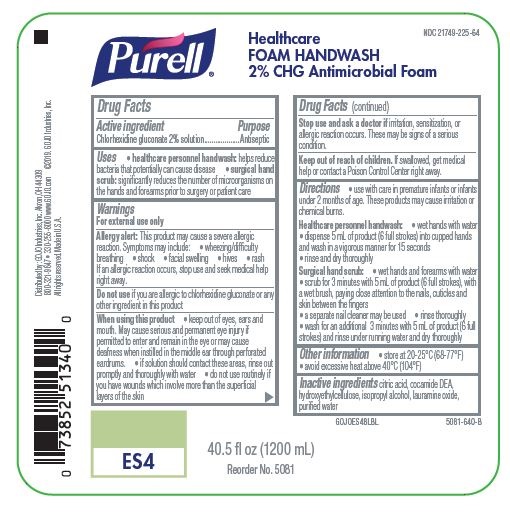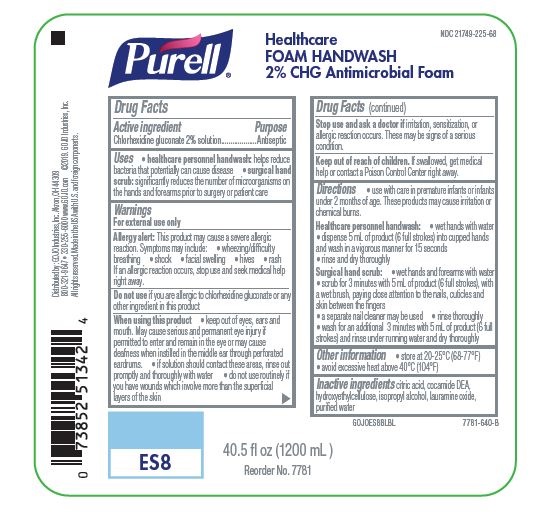 DRUG LABEL: Purell Antimicrobial Foam
NDC: 21749-225 | Form: LIQUID
Manufacturer: GOJO Industries, Inc.
Category: otc | Type: HUMAN OTC DRUG LABEL
Date: 20241221

ACTIVE INGREDIENTS: CHLORHEXIDINE GLUCONATE 20 mg/1 mL
INACTIVE INGREDIENTS: CITRIC ACID MONOHYDRATE; ISOPROPYL ALCOHOL; WATER; COCO DIETHANOLAMIDE; HYDROXYETHYL CELLULOSE (2000 CPS AT 1%); LAURAMINE OXIDE

Purell CS/ES System 2% CHG

Drug Facts

Active ingredient

chlorhexidine gluconate 2% solution

Purpose

Antiseptic

Uses

healthare personnel handwash: helps reduce bacteria that can potentially cause disease

surgical hand scrub: significantly reduces the number of microorganisms on the hands and forearms prior to surgery or patient care

Warnings

For external use only

Allergy alert:

This product may cause severe allergic reaction. Symptoms may include:

wheezing/difficulty breathing

shock

facial swelling

hives

rash

If an allergic reaction occurs, stop use and seek medical help right away.

Do not use

if you are allergic to chlorhexidine gluconate or any other ingredient in this product

When using this product

keep out of eyes, ears and mouth. May cause serious and permenant eye injury if permitted to enter and remain in the eye or may cause deafness when instilled in the middle ear through perforated eardrums.

if solution should contact these areas, rinse out promptly and thoroughly with water

do not use routinely if you have wounds which involve more than the superficial layers of the skin

Stop use and ask a doctor if

irritation, sensitization. or allergic reaction occurs. These may be signs of a serious condition.

Keep out of reach of children

If swallowed, get medical help or contact a Poison Control Center right away.

Directions

use with care in premature infants or infants under 2 months of age. These products may cause irritation or chemical burns.

Healthcare personnel handwash:

wet hands with water

dispense 5mL of product (6 full strokes) into cupped hands and wash in a vigorous manner for 15 seconds

rinse and dry throughly

Surgical hand scrub:

wet hands and forearms with water

scrub for 3 minutes with 5mL of product (6 full strokes), with a wet brush, paying close attention to the nails, cuticles and skin between the fingers

a seperate nail cleaner may be used

rinse thoroughly

wash for an additional 3 minutes with 5mL of product (6 full strokes) and rinse under running water and dry throughly

Other information

store at 20-25°C (68-77°F)

avoid excessive heat above 40°C (104°F)

Inactive ingredients

citric acid, comide DEA, hydroxyethylcellulose, isopropyl alcohol, lauramine oxide. purified water

PACKAGE LABEL

Purell

Healthcare

FOAM HANDWASH

2% CHG

Antimicrobial Foam

GOJOCSFLBLA

7887-641-F

NDC 21749-225-58

Purell

Healthcare FOAM HANDWASH 2% CHG

Antimicrobial Foam

Distributed by: GOJO Industries, Inc. Akron, OH 44309

800-321-9647 • 330-255-6000 www.GOJO.com ©2019, GOJO Industries, Inc.

All rights reserved. Made in U.S.A.

GOJOCS4BLBLA

5181-642-ES-B

42 fl oz (1250 mL)

NDC 21749-225-57

Purell

Healthcare FOAM HANDWASH 2% CHG

Antimicrobial Foam

Distributed by: GOJO Industries, Inc. Akron, OH 44309

800-321-9647 • 330-255-6000 www. GOJO.com ©2019. GOJO Industries, Inc.

All rights reserved. Made in U.S.A.

GOJOCS6BLBLA

6581-642-ES-B

40.5 FL OZ (1200 mL)

NDC 21749-225-56

Purell

Healthcare FOAM HANDWASH 2% CHG

Antimicrobial Foam

Distributed by: GOJO Industries, Inc. Akron, OH 44309

800-321-9647 • 330-255-6000 www.GOJO.com ©2019. GOJO Industries, Inc.

All rights reserved. Made in the USA with U.S. and foreign components

GOJOCS8BLBLA

7881-641-ES-B

40.5 FL OZ (1200 mL)

PACKAGE LABEL

HEALTHCARE

PURELL

FOAM

HANDWASH

CHLORHEXIDINE GLUCONATE

2% SOLUTION - ANTISEPTIC

40.5 fl oz (1200 mL)

GOJOESFLBL

7781-640-F

NDC 21749-225-64

Purell

Healthcare

FOAM HANDWASH

2% CHG Antimicrobial Foam

40.5 fl oz (1200 mL)

GOJOES4BLBL

5081-640-B

NDC 21749-225-68

Purell

Healthcare

FOAM HANDWASH

2% CHG Antimicrobial Foam

40.5 fl oz (1200 mL)

GOJOES8BLBL

7781-640-B